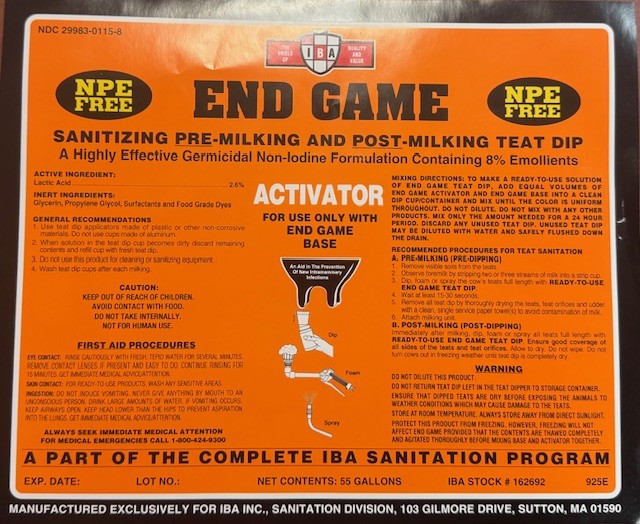 DRUG LABEL: END GAME ACITIVATOR
NDC: 29983-0115 | Form: SOLUTION
Manufacturer: IBA
Category: animal | Type: OTC ANIMAL DRUG LABEL
Date: 20251001

ACTIVE INGREDIENTS: LACTIC ACID 26 g/1 L
INACTIVE INGREDIENTS: SODIUM LAURYLGLUCOSIDE HYDROXYPROPYLSULFONATE; SODIUM BENZOATE; UREA; PROPYLENE GLYCOL

END GAME SANITIZING PRE-MILKING AND POST-MILKING TEAT DIP A HIGHLY EFFECTIVE GERMICIDAL NON-IODINE FORMULATION CONTAINING 8% Emollients

ACTIVE INGREDIENT

Lactic Acid...........2.6%

INERT INGREDIENTS
Glycerin, Propylene Glycol, Surfactants and Food Grade Dyes

INDICATIONS AND USAGE

GENERAL RECOMMENDATIONS

To make a ready-to-use solution of END GAME teat dip, add equal volumes of END GAME Activator and END GAME Base into a clean dip cup/container and mix until the color is uniform throughout. Do not dilute. Do not mix with any other products. Mix only the amount needed for a 24 hour period. Discard any unused teat dip. Unused teat dip may be diluted with water and safely flushed down the drain.

RECOMMENDED PROCEDURES FOR TEAT SANITATION
A. PRE-MILKING (PRE-DIPPING)
1. Remove visible soils from the teats
2. Observe foremilk by stripping two or three streams of milk into a strip cup.
3. Dip or spray the cow's teats full length with READY-TO-USE END GAME TEAT DIP.
4. Wait at least 15-30 seconds.
5. Remove all teat dip by thoroughly drying the teats, teat orifices and udder with a clean, single service paper towel(s) to avoid contamination
of milk.
6. Attach milking unit.
B. POST-MILKING (POST-DIPPING)
Immediately after milking, dip or spray all teats full length with READY-TO-USE END GAME TEAT DIP. Ensure good coverage of all sides of the teats and teat orifices. Allow to dry. Do not wipe. Do not turn cows out in freezing weather until teat dip is completely dry.

WARNING

Do not dilute this product.
Do not return teat dip left in the teat dipper to storage container.
Ensure that dipped teats are dry before exposing the animals to weather conditions which may cause damage to the teats.
Store at room temperature. Always store away from direct sunlight.

Protect this product from freezing. However, freezing will not affect PRO-SAN ACTIVATOR provided that the contents are thawed completely and agitated thoroughly before mixing base and activator together.

CAUTION: KEEP OUT OF REACH OF CHILDREN.
AVOID CONTACT WITH FOOD. DO NOT TAKE INTERNALLY.

FIRST AID PROCEDURES

EYE CONTACT: Rinse cautiously with fresh, tepid water for several minutes. Remove contact lenses if present and easy to do. Continue rinsing for 15 minutes. Get immediate medical advice/attention. SKIN CONTACT: For RTU products wash any sensitive areas. INGESTION: Do not induce vomiting. Never give anything by mouth to an unconscious person. Drink large amounts of water. If vomiting occurs, keep airways open. Keep head lower than the hips to prevent aspiration into the lungs. Get immediate medical advice/attention.

ALWAYS SEEK IMMEDIATE MEDICAL ATTENTION

FOR MEDICAL EMERGENCIES CALL 1-800-424-9300